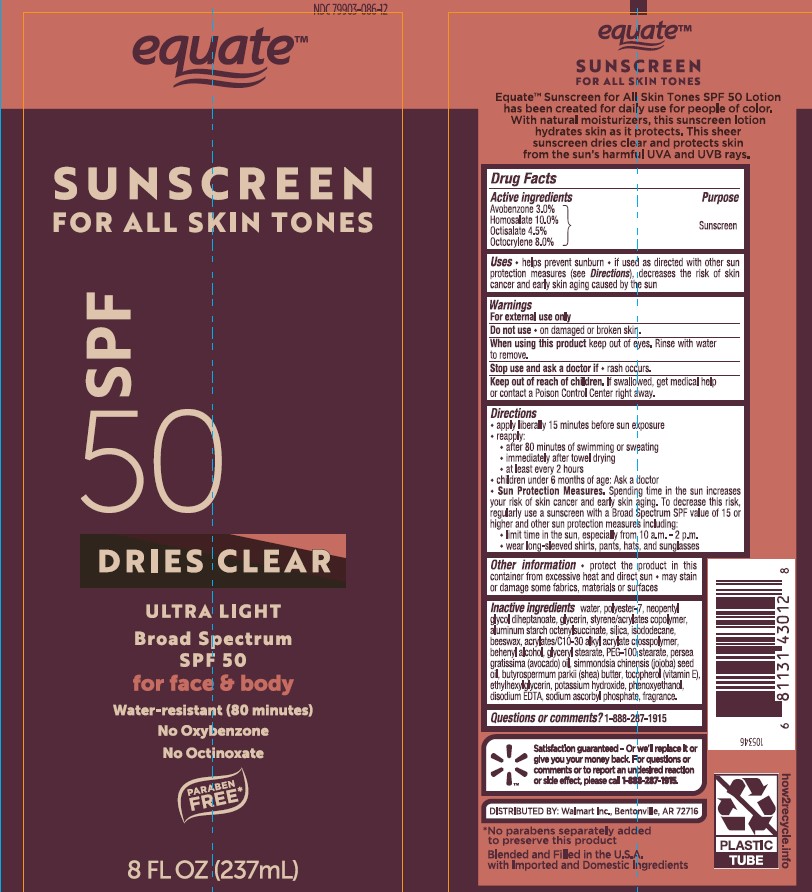 DRUG LABEL: Equate Sunscreen for All Skin Tones SPF 50
NDC: 79903-086 | Form: LOTION
Manufacturer: Wal-Mart Stores Inc
Category: otc | Type: HUMAN OTC DRUG LABEL
Date: 20241023

ACTIVE INGREDIENTS: AVOBENZONE 30 mg/1 mL; HOMOSALATE 100 mg/1 mL; OCTISALATE 45 mg/1 mL; OCTOCRYLENE 80 mg/1 mL
INACTIVE INGREDIENTS: WATER; POLYESTER-7; NEOPENTYL GLYCOL DIHEPTANOATE; GLYCERIN; STYRENE/ACRYLAMIDE COPOLYMER (500000 MW); ALUMINUM STARCH OCTENYLSUCCINATE; SILICON DIOXIDE; PHENOXYETHANOL; ISODODECANE; ETHYLHEXYLGLYCERIN; (C10-C30)ALKYL METHACRYLATE ESTER; TOCOPHEROL; GLYCERYL STEARATE SE; PEG-100 STEARATE; POTASSIUM HYDROXIDE; EDETATE DISODIUM ANHYDROUS; SODIUM ASCORBYL PHOSPHATE; YELLOW WAX; DOCOSANOL; AVOCADO OIL; JOJOBA OIL; SHEA BUTTER

Equate Sunscreen for All Skin Tones SPF 50

Active Ingredients

Avobenzone 3.0%
Homosalate 10.0%
Octisalate 4.5%
Octocrylene 8.0%

Purpose

Sunscreen

Uses

• helps prevent sunburn
• if used as directed with other sun protection measures (see Directions), decreases the risk of skin cancer and early skin aging caused by the sun

Warnings

For external use only

Do not use

• on damaged or broken skin.

When using this product

• keep out of eyes. Rinse with water to remove.

Stop use and ask a doctor if

rash occurs.

Keep out of reach of children

If swallowed, get medical help or contact a Poison Control Center right away

Directions

• apply liberally 15 minutes before sun exposure
• reapply:
• after 80 minutes of swimming or sweating
• immediately after towel drying
• at least every 2 hours
• children under 6 months of age: Ask a doctor
• Sun Protection Measures. Spending time in the sun increases your risk of skin cancer and early skin aging. To decrease this risk, regularly use a sunscreen with a Broad Spectrum SPF value of 15 or higher and other sun protection measures including:
• limit time in the sun, especially from 10 a.m. - 2 p.m.
• wear long-sleeved shirts, pants, hats, and sunglasses

Other information

• protect the product in this container from excessive heat and direct sun
• may stain or damage some fabrics, materials or surfaces

Inactive Ingredients

water, polyester-7, neopentyl glycol diheptanoate, glycerin, styrene/acrylates copolymer, aluminum starch octenylsuccinate, silica, phenoxyethanol, isododecane, arachidyl alcohol, beeswax, ethylhexylglycerin, acrylates/C10-30 alkyl acrylate crosspolymer, behenyl alcohol, tocopherol (vitamin E), arachidyl glucoside, glyceryl stearate, PEG-100 stearate, potassium hydroxide, disodium EDTA, sodium ascorbyl phosphate, fragrance.